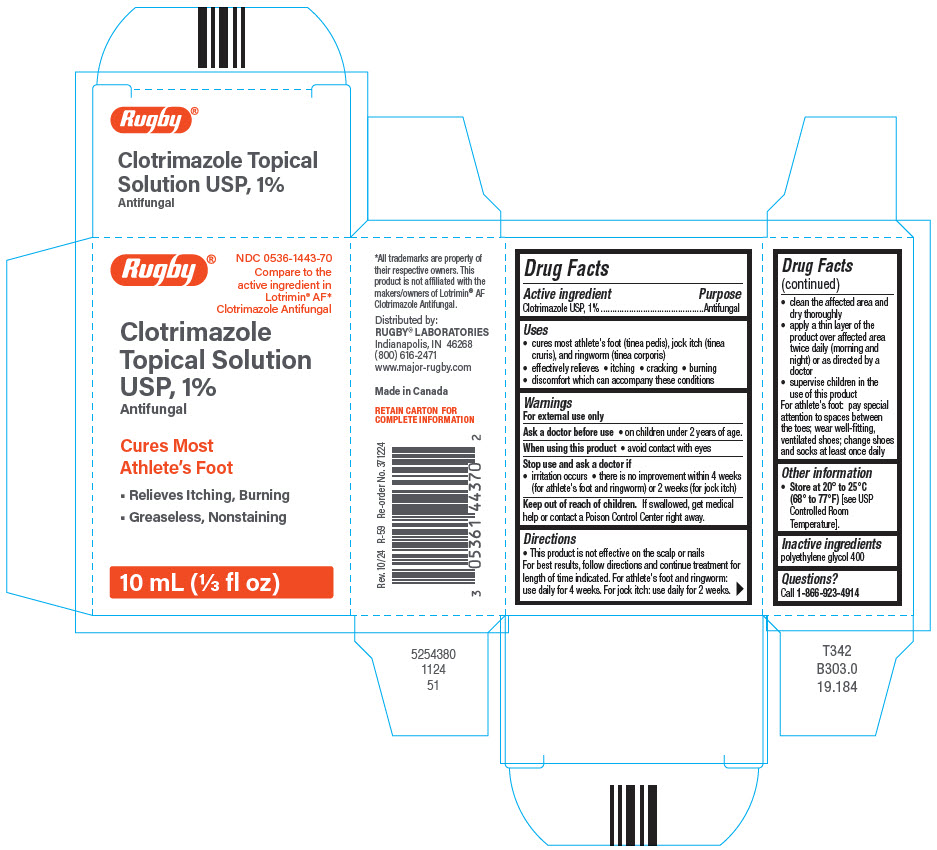 DRUG LABEL: CLOTRIMAZOLE
NDC: 0536-1443 | Form: SOLUTION
Manufacturer: Rugby Laboratories, Inc.
Category: otc | Type: HUMAN OTC DRUG LABEL
Date: 20250709

ACTIVE INGREDIENTS: CLOTRIMAZOLE 1 g/100 mL
INACTIVE INGREDIENTS: POLYETHYLENE GLYCOL 400

Clotrimazole Topical Solution USP, 1%

Drug Facts

Active ingredient

Clotrimazole USP, 1%

Purpose

Antifungal

Uses

- cures most athlete's foot (tinea pedis), jock itch (tinea cruris), and ringworm (tinea corporis)
- effectively relieves
  - itching
  - cracking
  - burning
  - discomfort which can accompany these conditions

Warnings

For external use only

Ask a doctor before use

- on children under 2 years of age.

When using this product

- avoid contact with eyes

Stop use and ask a doctor if

- irritation occurs
- there is no improvement within 4 weeks (for athlete's foot and ringworm) or 2 weeks (for jock itch)

Keep out of reach of children.If swallowed, get medical help or contact a Poison Control Center right away.

Directions

- This product is not effective on the scalp or nails
  For best results, follow directions and continue treatment for length of time indicated. For athlete's foot and ringworm: use daily for 4 weeks. For jock itch: use daily for 2 weeks.
- clean the affected area and dry thoroughly
- apply a thin layer of the product over affected area twice daily (morning and night) or as directed by a doctor
- supervise children in the use of this product

For athlete's foot: pay special attention to spaces between the toes; wear well-fitting, ventilated shoes; change shoes and socks at least once daily

Other information

- Store at 20° to 25°C (68° to 77°F)[see USP Controlled Room Temperature].

Inactive ingredients

polyethylene glycol 400

Questions?

Call 1-866-923-4914

Distributed by:
RUGBY®LABORATORIES
Indianapolis, IN 46268

PRINCIPAL DISPLAY PANEL - 10 mL Bottle Carton

Rugby®

NDC 0536-1443-70
Compare to the
active ingredient in
Lotrimin®AF*
Clotrimazole Antifungal

Clotrimazole
Topical Solution
USP, 1%
Antifungal

Cures Most
Athlete's Foot

- Relieves Itching, Burning
- Greaseless, Nonstaining

10 mL (⅓ fl oz)